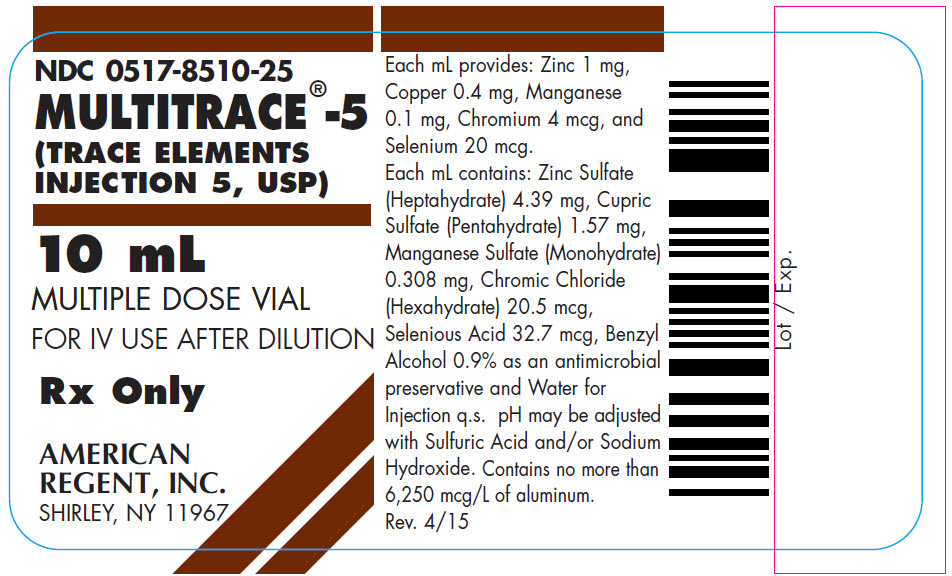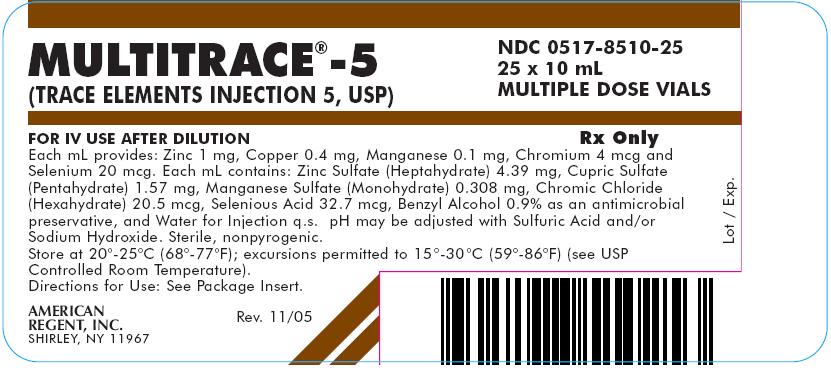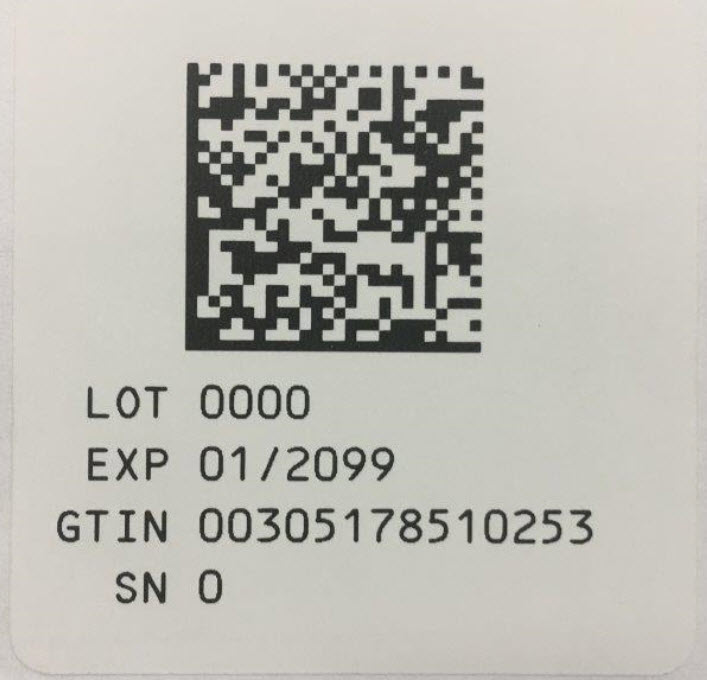 DRUG LABEL: Multitrace-5
NDC: 0517-8510 | Form: INJECTION, SOLUTION
Manufacturer: American Regent, Inc.
Category: prescription | Type: HUMAN PRESCRIPTION DRUG LABEL
Date: 20190425

ACTIVE INGREDIENTS: ZINC SULFATE HEPTAHYDRATE 4.39 mg/1 mL; CUPRIC SULFATE 1.57 mg/1 mL; MANGANESE SULFATE 0.308 mg/1 mL; CHROMIC CHLORIDE 20.5 ug/1 mL; SELENIOUS ACID 32.7 ug/1 mL
INACTIVE INGREDIENTS: BENZYL ALCOHOL; SULFURIC ACID; SODIUM HYDROXIDE; WATER

MULTITRACE®- 5 (TRACE ELEMENTS INJECTION 5, USP)

FOR IV USE AFTER DILUTION

Rx Only

DESCRIPTION

MULTITRACE® - 5 (TRACE ELEMENTS INJECTION 5, USP) is a sterile nonpyrogenic solution containing five Trace Elements for use as an additive for Total Parenteral Nutrition (TPN).

Each mL provides: Zinc 1 mg, Copper 0.4 mg, Manganese 0.1 mg, Chromium 4 mcg and Selenium 20 mcg.

Each mL Contains: Zinc Sulfate Heptahydrate 4.39 mg (equivalent to 1 mg Zinc); Cupric Sulfate Pentahydrate 1.57 mg (equivalent to 0.4 mg Copper); Manganese Sulfate Monohydrate 0.308 mg (equivalent to 0.1 mg Manganese); Chromic Chloride Hexahydrate 20.5 mcg (equivalent to 4 mcg Chromium); Selenious Acid 32.7 mcg (equivalent to 20 mcg Selenium); and Water for Injection q.s. pH may be adjusted with Sulfuric Acid and/or Sodium Hydroxide. 0.9% Benzyl Alcohol added as an antimicrobial preservative.

CLINICAL PHARMACOLOGY

ZINC has been identified as a cofactor for over 70 different enzymes, including alkaline phosphatase, lactic dehydrogenase and both RNA and DNA polymerase. Zinc facilitates wound healing, helps maintain normal growth rates, normal skin hydration and senses of taste and smell.

Providing zinc during TPN prevents development of the following deficiency symptoms: parakeratosis, hypogeusia, anorexia, dysosmia, geophagia, hypogonadism, growth retardation and hepatosplenomegaly. At plasma levels below 20 mcg zinc/100 mL, dermatitis followed by alopecia has been reported for TPN patients.

COPPER is essential as a cofactor for serum ceruloplasmin, an oxidase necessary for proper formation of the iron carrier protein, transferrin. Copper also helps maintain normal rates of red and white blood cell formation. Scorbutic type bone changes seen in infants fed exclusively with copper-poor cow's milk are believed due to decreased activity of ascorbate oxidase, a cuproenzyme.

Providing copper during TPN prevents development of the following deficiency symptoms: leukopenia, neutropenia, anemia, depressed ceruloplasmin levels, impaired transferrin formation and secondary iron deficiency.

MANGANESE is an activator for enzymes such as polysaccharide polymerase, liver arginase, cholinesterase and pyruvate carboxylase.

Providing manganese during TPN prevents development of the following deficiency symptoms: nausea and vomiting, weight loss, dermatitis, and changes in growth and color of hair.

CHROMIUM (trivalent) is part of glucose tolerance factor, an activator of insulin-mediated reactions. Chromium helps to maintain normal glucose metabolism and peripheral nerve function.

Providing chromium during TPN prevents development of the following deficiency symptoms: impaired glucose tolerance, ataxia, peripheral neuropathy and a confusional state similar to mild/moderate hepatic encephalopathy.

SELENIUM is part of glutathione peroxidase which protects cell components from oxidative damage due to peroxides produced in cellular metabolism.

Prolonged TPN support in humans has resulted in selenium deficiency symptoms which include muscle pain and tenderness. The symptoms have been reported to respond to supplementation of TPN solutions with selenium.

INDICATIONS AND USAGE

This formulation is indicated for use as a supplement to intravenous solutions given for TPN. Administration of the solution in TPN solutions helps to maintain plasma levels of zinc, copper, manganese, selenium and chromium and to prevent depletion of endogenous stores of these trace elements and subsequent deficiency symptoms.

CONTRAINDICATIONS

MULTITRACE® - 5 should not be given undiluted by direct injection into a peripheral vein because of the potential of infusion phlebitis.

WARNINGS

Copper and Manganese are eliminated via the bile. In patients with severe liver dysfunction and/or biliary tract obstruction, decreasing or omitting copper and manganese supplements entirely may be necessary.

This product contains aluminum that may be toxic. Aluminum may reach toxic levels with prolonged parenteral administration if kidney function is impaired. Premature neonates are particularly at risk because their kidneys are immature, and they require large amounts of calcium and phosphate solutions, which contain aluminum.

Research indicates that patients with impaired kidney function, including premature neonates, who receive parenteral levels of aluminum at greater than 4 to 5 mcg/kg/day accumulate aluminum at levels associated with central nervous system and bone toxicity. Tissue loading may occur at even lower rates of administration.

PRECAUTIONS

Before administering MULTITRACE® - 5 in TPN solutions, the physician must assess the metabolic requirements for trace elements and disease state of the patient. Frequent determinations of serum levels of the various trace elements are suggested as a guideline for adjusting the dosage or completely omitting the solution. ZINC is eliminated via the intestine and kidneys. The possibility of retention should be considered in patients with malfunctioning excretory routes. COPPER and MANGANESE are eliminated via the bile, therefore the possibility of retention of these elements should be considered in patients with biliary obstruction. Ancillary routes of MANGANESE excretion, however, include pancreatic juice, or reabsorption into the lumen of duodenum, jejunum, or ileum.

In assessing the contribution of CHROMIUM supplements to maintenance of normal glucose homeostasis, consideration should be given to the possibility that the patient may be diabetic, in which case oral or intravenous antidiabetic medication may be indicated.

As SELENIUM is eliminated in urine and feces, SELENIUM supplements may be adjusted, reduced or omitted in renal dysfunction and/or gastrointestinal malfunction. In patients receiving blood transfusions, contribution from such transfusions should also be considered. Frequent selenium plasma level determinations are suggested as a guideline.

In animals, SELENIUM has been reported to enhance the action of Vitamin E and decrease the toxicity of mercury, cadmium, and arsenic.

Pregnancy

Teratogenic Effects

Pregnancy Category C: SELENIUM at high dosage levels (15-30 mcg/egg) has been reported to have adverse embryological effects among chickens. There are however no adequate and wellcontrolled studies in pregnant women. MULTITRACE® - 5 should be used during pregnancy only if potential benefit justifies the potential risk to the fetus.

Presence of SELENIUM in placenta and umbilical cord blood has been reported in humans.

ADVERSE REACTIONS

The amounts of ZINC, COPPER, MANGANESE, CHROMIUM and SELENIUM in the solution are very small and toxicity symptoms due to these trace elements at suggested dosage levels are considered unlikely to occur.

OVERDOSAGE

Symptoms of ZINC overdosage resulting from oral ingestion of Zinc Sulfate in large amounts have resulted in death. Symptoms included nausea, vomiting, dehydration, electrolyte imbalances, dizziness, abdominal pain, lethargy and incoordination. Single intravenous doses of 1 to 2 mg zinc/kg body weight have been given to adult leukemic patients without toxic manifestations. Normal plasma levels for Zinc vary from approximately 88 to 112 mcg/100 mL. Plasma levels sufficient to produce symptoms of toxic manifestations are not known. Calcium supplements may confer a protective effect against Zinc toxicity.

Symptoms of COPPER toxicity reported in literature include prostration, behavior change, diarrhea, progressive marasmus, hypotonia, photophobia and peripheral edema. D-penicillamine has been reported effective as an antidote.

MANGANESE toxicity has not been reported in patients receiving TPN. Neither have reports of manganese toxicity from excessive intake in foods and/or beverages been published.

Symptoms of CHROMIUM toxicity include nausea, vomiting, ulcers of gastrointestinal tract, renal and hepatic damage, and abnormalities of the central nervous system culminating in convulsions and coma. Trivalent Chromium administered intravenously to TPN patients has been shown to be nontoxic when given at dosage levels up to 250 mcg/day for two consecutive weeks.

Chronic toxicity in humans resulting from exposure to SELENIUM in industrial environments, intake of foods grown in seleniferous soils, use of selenium contaminated water, and application of cosmetics containing selenium has been reported in literature. Toxicity symptoms include hair loss, weakened nails, dermatitis, dental defects, gastrointestinal disorders, nervousness, mental depression, metallic taste, vomiting, and garlic odor of breath and sweat. Acute poisoning due to ingestion of large amounts of selenium compounds has resulted in death with histopathological changes including fulminating peripheral vascular collapse, internal vascular congestion, diffusely hemorrhagic, congested and edematous lungs, brick-red color gastric mucosa. The death was preceded by coma. No effective antidote to selenium poisoning in humans is known. Animal studies have shown casein and linseed oil in feeds, reduced glutathione, arsenic, magnesium sulfate, and bromobenzene to afford limited protection.

DOSAGE AND ADMINISTRATION

Each mL of the solution provides Zinc 1 mg, Copper 0.4 mg, Manganese 0.1 mg, Chromium 4 mcg, and Selenium 20 mcg. The suggested dosage ranges for the five trace elements are:

ZINC: For the metabolically stable adult receiving TPN, the suggested intravenous dosage level is 2.5 to 4 mg zinc/day. An additional 2 mg zinc/day is suggested for acute catabolic states. For the stable adult with fluid loss from the small bowel, an additional 12.2 mg zinc/liter of small bowel fluid lost, or an additional 17.1 mg zinc/kg of stool or ileostomy output is recommended. Frequent monitoring of zinc blood levels is suggested for patients receiving more than the usual maintenance dosage level of zinc. Normal plasma levels for zinc vary from approximately 88 to 112 mcg/100 mL.

For full term infants and children up to 5 years of age, 100 mcg zinc/kg/day is recommended. For premature infants (birth weight less than 1500 g) up to 3 kg in body weight, 300 mcg zinc/kg/day is suggested.

COPPER: For the metabolically stable adult receiving TPN, the suggested additive dosage level is 0.5 to 1.5 mg copper/day. For pediatric patients, the suggested additive dosage level is 20 mcg copper/kg/day. The normal plasma range for copper is approximately 80 to 160 mcg/100 mL.

MANGANESE: For the metabolically stable adult receiving TPN, the suggested additive dosage level for manganese is 0.15 mg to 0.8 mg/day. For pediatric patients, a dosage level of 2 to 10 mcg manganese/kg/day is recommended.

CHROMIUM: For the metabolically stable adult receiving TPN, the suggested additive dosage level is 10 to 15 mcg chromium/day. The metabolically stable adult with intestinal fluid loss may require 20 mcg chromium/day, with frequent monitoring of blood levels as a guideline for subsequent administration. For pediatric patients, the suggested additive dosage level is 0.14 to 0.20 mcg/kg/day.

SELENIUM: For metabolically stable adults receiving TPN, the suggested additive dosage level is 20 to 40 mcg selenium/day. For pediatric patients, the suggested additive dosage level is 3 mcg/kg/day.

In adults, selenium deficiency states resulting from long term TPN support, selenium as selenomethionine or selenious acid, administered intravenously at 100 mcg/day for a period of 24 and 31 days, respectively, has been reported to reverse deficiency symptoms without toxicity. The normal whole blood range for selenium is approximately 10 to 37 mcg/100 mL.

Periodic monitoring of plasma levels of Zinc, Copper, Manganese, Chromium and Selenium is suggested as a guideline for administration.

Aseptic addition of MULTITRACE® - 5 to parenteral nutrition solutions under laminar flow hood is recommended. The trace elements present in MULTITRACE® - 5 are physically compatible with the electrolytes and vitamins usually present in parenteral nutrition formulations.

Do not directly mix ascorbic acid injection with copper or selenium containing parenteral products in the same syringe or vial, as this admixture may cause the formation of an insoluble precipitate.

Parenteral drug products should be inspected visually for particulate matter and discoloration prior to administration, whenever solution and container permit.

Store at 20° to 25°C (68° to 77°F); excursions permitted to 15° to 30°C (59° to 86°F) (See USP Controlled Room Temperature).

HOW SUPPLIED

MULTITRACE® - 5 (TRACE ELEMENTS INJECTION 5, USP)

Each mL provides: Zinc 1 mg, Copper 0.4 mg, Manganese 0.1 mg, Chromium 4 mcg, Selenium 20 mcg.

NDC 0517-8510-25 10 mL Multiple Dose Vial* Packaged in boxes of 25

*Contains 0.9% benzyl alcohol as an antimicrobial preservative.

AMERICAN
REGENT, INC.
SHIRLEY, NY 11967

IN8510
Rev. 8/18

PACKAGE LABEL.PRINCIPAL DISPLAY PANEL

Container
NDC 0517-8510-25
MULTITRACE®-5
(TRACE ELEMENTS INJECTION 5, USP)

10 mL
MULTIPLE DOSE VIAL

FOR IV USE AFTER DILUTION

Rx Only

Carton

MULTITRACE®-5
(TRACE ELEMENTS INJECTION 5, USP)

NDC 0517-8510-25
25 x 10 mL
MULTIPLE DOSE VIALS

FOR IV USE AFTER DILUTION

Rx Only

Each mL provides: Zinc 1 mg, Copper 0.4 mg, Manganese 0.1 mg, Chromium 4 mcg and Selenium 20 mcg. Each mL contains: Zinc Sulfate (Heptahydrate) 4.39 mg, Cupric Sulfate (Pentahydrate) 1.57 mg, Manganese Sulfate (Monohydrate) 0.308 mg, Chromic Chloride (Hexahydrate) 20.5 mcg, Selenious Acid 32.7 mcg, Benzyl Alcohol 0.9% as an antimicrobial preservative, and Water for Injection q.s. pH may be adjusted with Sulfuric Acid and/or Sodium Hydroxide. Sterile, nonpyrogenic.
Store at 20°-25°C (68°-77°F); excursions permitted to 15 °-30 °C (59°-86°F) (see USP Controlled Room Temperature).
Directions for Use: See Package Insert.

AMERICAN
REGENT, INC.
SHIRLEY, NY 11967

Rev. 11/05